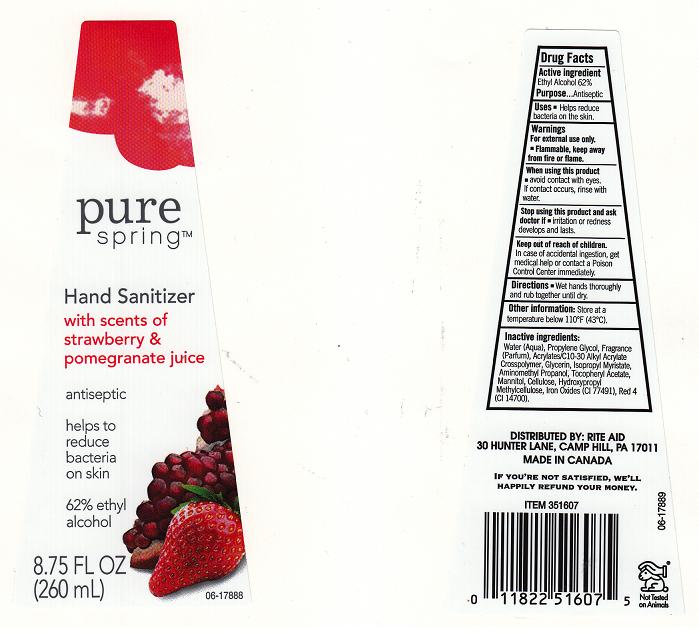 DRUG LABEL: PURE SPRING
NDC: 11822-4660 | Form: LIQUID
Manufacturer: RITE AID CORPORATION
Category: otc | Type: HUMAN OTC DRUG LABEL
Date: 20120319

ACTIVE INGREDIENTS: ALCOHOL 62 mL/100 mL
INACTIVE INGREDIENTS: WATER; PROPYLENE GLYCOL; CARBOMER COPOLYMER TYPE A; GLYCERIN; ISOPROPYL MYRISTATE; AMINOMETHYLPROPANOL; .ALPHA.-TOCOPHEROL ACETATE; MANNITOL; .ALPHA.-CELLULOSE; HYPROMELLOSE 2208 (100 MPA.S); FERRIC OXIDE RED; FD&C RED NO. 4

DRUG FACTS BOX

ACTIVE INGREDIENT

ETHYL ALCOHOL 62%

PURPOSE

ANTISEPTIC

USES

HELPS REDUCE BACTERIA ON THE SKIN

WARNINGS

FOR EXTERNAL USE ONLY. FLAMMABLE. KEEP AWAY FROM FIRE OR FLAME.

WHEN USING THIS PRODUCT

AVOID CONTACT WITH EYES. IF CONTACT OCCURS, RINSE WITH WATER.

STOP USING THIS PRODUCT AND ASK DOCTOR IF

IRRITATION OR REDNESS DEVELOPS AND LASTS.

KEEP OUT OF REACH OF CHILDREN

IN CASE OF ACCIDENTAL INGESTION, GET MEDICAL HELP HELP OR CONTACT A POISON CONTROL IMMEDIATELY.

DIRECTIONS

WET HANDS THOROUGHLY AND RUB TOGETHER UNTIL DRY.

OTHER INFORMATION

KEEP BELOW 110F (43C)

INACTIVE INGREDIENTS

WATER (AQUA), PROPYLENE GLYCOL, FRAGRANCE (PARFUM), ACRYLATES /C10-30 ALKYL ACRYLATE CROSSPOLMER, GLYCERIN, ISOPROPYL MYRISTATE, AMINOMETHYL PROPANOL, TOCOPHERYL ACETATE, MANNITOL, CELLULOSE, HYDROXYPROPYL METHYLCELLULOSE,IRON OXIDES (CI77491), RED 4 (CI 14700)